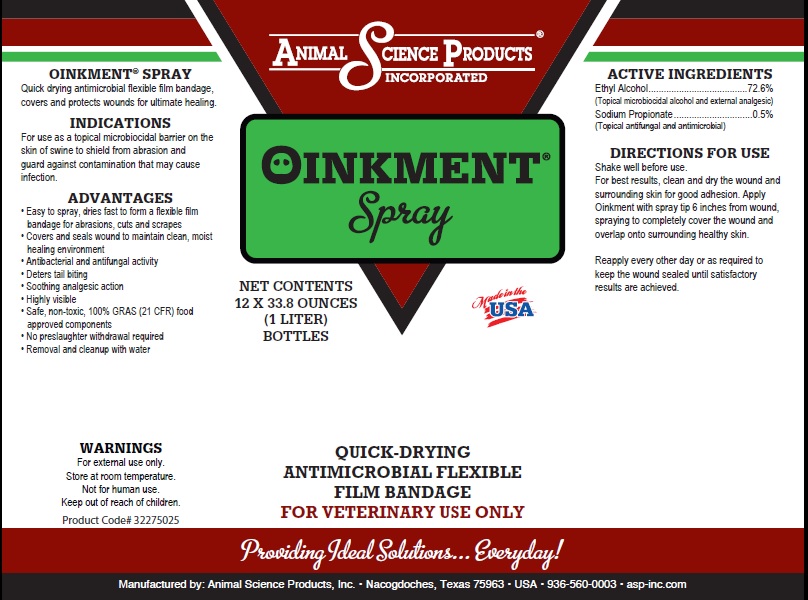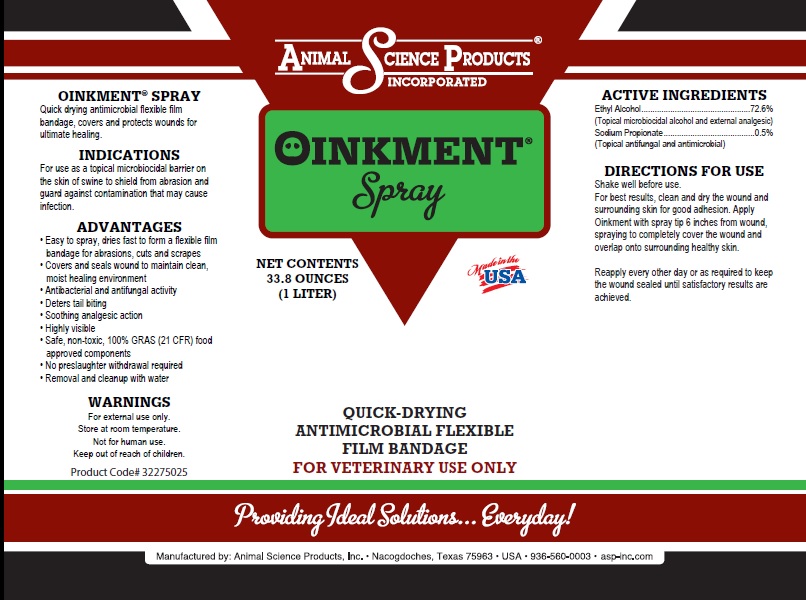 DRUG LABEL: Oinkment
NDC: 57932-005 | Form: LIQUID
Manufacturer: Animal Science Products, Inc.
Category: animal | Type: OTC ANIMAL DRUG LABEL
Date: 20251028

ACTIVE INGREDIENTS: ALCOHOL 7.2 mg/1 mL; SODIUM PROPIONATE 0.5 mg/1 mL
INACTIVE INGREDIENTS: WATER; ANHYDROUS CITRIC ACID; METHYLCELLULOSE, UNSPECIFIED; FD&C YELLOW NO. 5; FD&C BLUE NO. 1

Oinkment

Active Ingredient

Ethyl Alcohol.......................................72.6%
Sodium Propionate...............................0.5%

Purpose

QUICK-DRYING ANTIMICROBIAL FLEXIBLE FILM BANDAGE

FOR VETERINARY USE ONLY

Uses

For use as a topical microbiocidal barrier on the skin of swine to shield from abrasion and guard against contamination that may cause infection

Warnings

- For external use only.
- Store at room temperature.
- Not for human use.
- Keep out of reach of children.

Directions

Shake well before use. For best results, clean and dry the wound and surrounding skin for good adhesion. Apply Oinkment with spray tip 6 inches from wound, spraying to completely cover the wound and overlap onto surrounding healthy skin.

Reapply every other day or as required to keep the wound sealed until satisfactory.

ADVANTAGES

• Easy to spray, dries fast to form a flexible film bandage for abrasions, cuts and scrapes
• Covers and seals wound to maintain clean, moist healing environment
• Antibacterial and antifungal activity
• Deters tail biting
• Soothing analgesic action
• Highly visible
• Safe, non-toxic, 100% GRAS (21 CFR) food approved components
• No preslaughter withdrawal required
• Removal and cleanup with water

Inactive Ingredient

Anhydrous citric acid, Water, FD&C yellow no. 5, FD&C blue no. 1, Methylcellulose

Product label

Bottle label

Product label

Box label